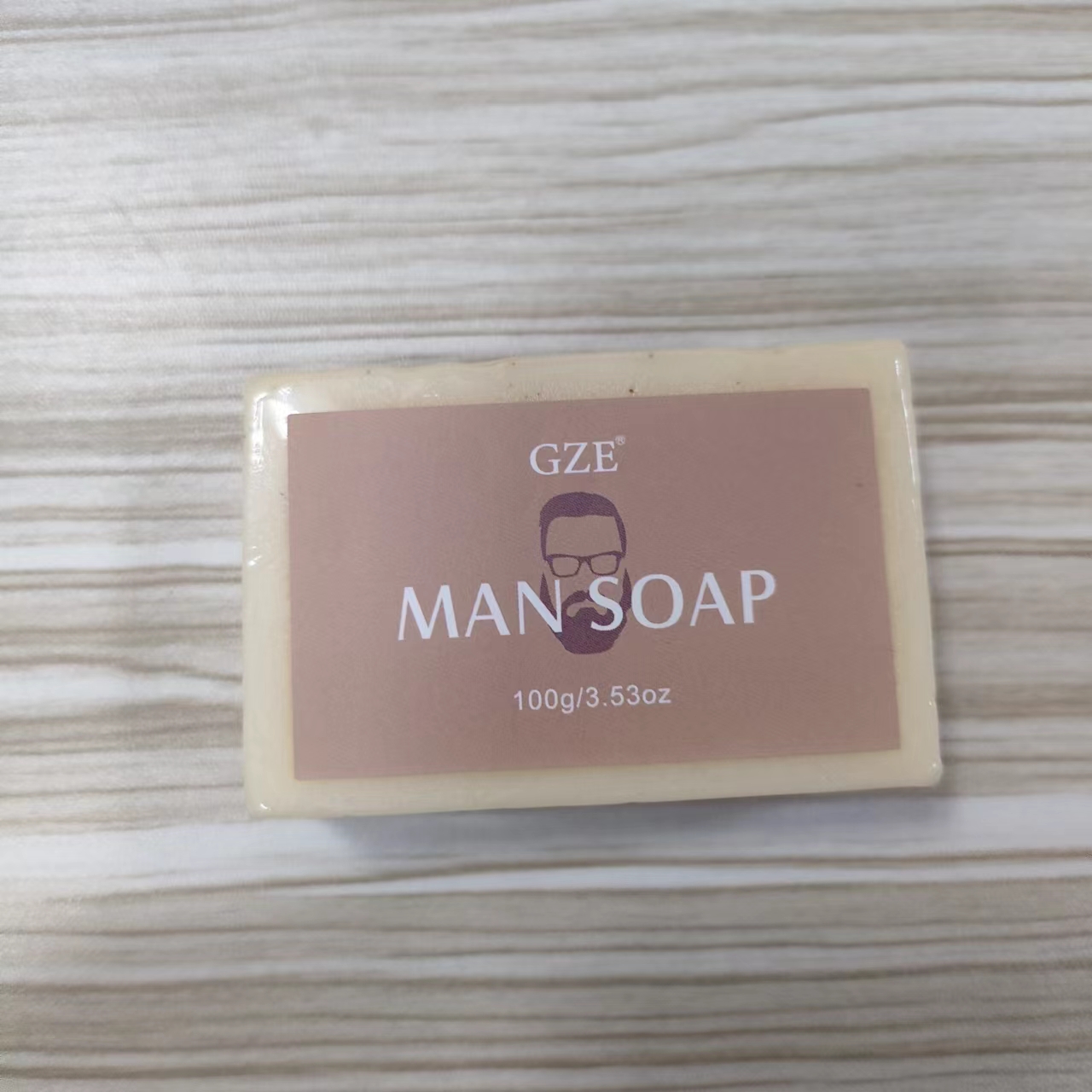 DRUG LABEL: GZE Man Saop
NDC: 74458-223 | Form: SOAP
Manufacturer: Guangzhou Yilong Cosmetics Co., Ltd
Category: otc | Type: HUMAN OTC DRUG LABEL
Date: 20241108

ACTIVE INGREDIENTS: AVENA SATIVA (OAT) BRAN 5 g/100 g
INACTIVE INGREDIENTS: GLYCERIN; FRAGRANCE 13576; SODIUM PALMATE; SODIUM CHLORIDE; SODIUM COCOATE; WATER

GZE MAN SOAP

INACTIVE INGREDIENT

Sodium Palmate

Sodium Cocoate

Water

Glycerin

Fragrance

Sodium Chloride

ACTIVE INGREDIENT

Avena Sativa (Oat) Bran

INDICATIONS AND USAGE

Wet soap bar under warm running water to create a rich lather. Massage lather onto your skin, then rinse away.

DOSAGE AND ADMINISTRATION

Wet soap bar under warm running water to create a rich lather. Massage lather onto your skin, then rinse away.

PURPOSE

Exfoliating.

WARNINGS

For external use only.

Stop use and ask a doctor if rash occurs.

Do not use on damaged or broken skin.

When using this product keep out of eyes. Rinse with water to remove.

Keep out of reach of children. If swallowed, get medical help or contact a Poison Control Center right away.